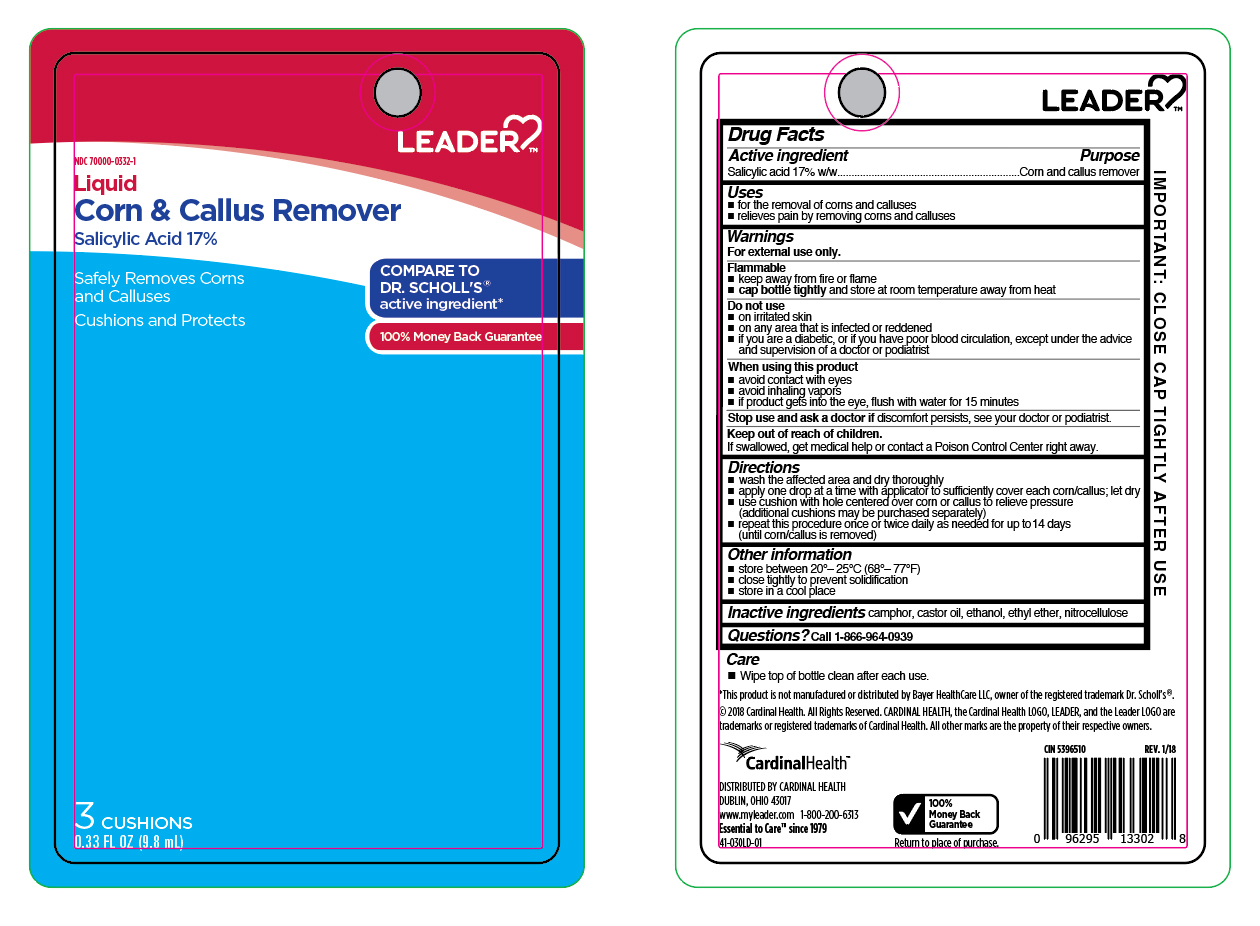 DRUG LABEL: Salicylic Acid
NDC: 70000-0332 | Form: LIQUID
Manufacturer: LEADER/ Cardinal Health 110, Inc.
Category: otc | Type: HUMAN OTC DRUG LABEL
Date: 20251231

ACTIVE INGREDIENTS: SALICYLIC ACID 17 g/100 mL
INACTIVE INGREDIENTS: ETHYL ETHER; PYROXYLIN; CAMPHOR (NATURAL); CASTOR OIL; ALCOHOL

Leader Liquid Corn and Callus Remover

Active ingredient

Salicylic acid 17%w/w

Purpose

Corn and callus remover

Uses

- for the removal of corns and calluses
- relieves pain by removing corns and calluses

Warnings

For external use only.

Flammable

- keep away from fire or flame
- cap bottle tightly and store at room temperature away heat

Do not use

- on irritated skin
- on any area that is infected or reddened
- if you are a diabetic, or if you have poor blood circulation, except under the advice and supervision of a doctor or podiatrist

When using this product

- avoid contact with eyes
- avoid inhaling vapors
- if product gets into the eyes, flush with water for 15 minutes

Keep out of reach of children.

If swallowed, get medical help or contact a Poison Control Center right away.

Directions

- wash affected area and dry thoroughly
- apply one drop at a time with applicator, to sufficiently cover each corn/callus; let dry
- use cushions with hole centered over corn or callus to relieve pressure (additional cushions may be purchased separately)
- repeat this procedure once or twice daily as needed for up to 14 days (until corn/callus is removed)

Other Information

- store between 20o-25oC (68o-77oF)
- close tightly to prevent solidification
- store in a cool place

Inactive ingredients

camphor, castro oil, ethanol, ethyl ether, nitrocellulose

Questions?

Call 1-800-200-6313

Principal Display Panel

LEADER

Liquid

Corn & Callus Remover
Salicylic Acid 17%

Safely Removes Corns

and Calluses

Cushions and Protects

3 Cushions

0.33 FL OZ (9.8 mL)